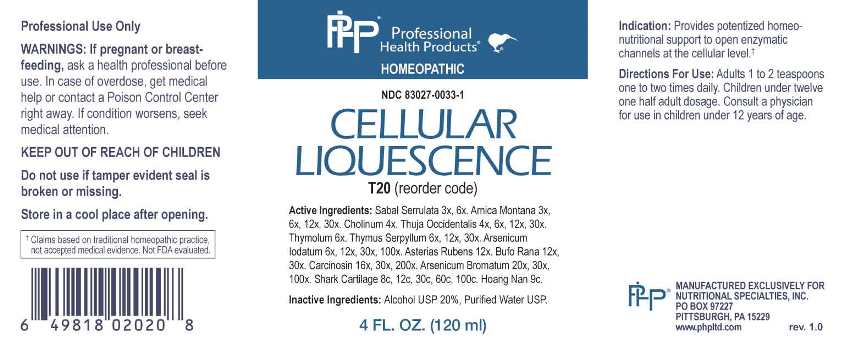 DRUG LABEL: Cellular Liquescence
NDC: 83027-0033 | Form: LIQUID
Manufacturer: Nutritional Specialties, Inc.
Category: homeopathic | Type: HUMAN OTC DRUG LABEL
Date: 20230417

ACTIVE INGREDIENTS: SAW PALMETTO 3 [hp_X]/1 mL; ARNICA MONTANA WHOLE 3 [hp_X]/1 mL; CHOLINE HYDROXIDE 4 [hp_X]/1 mL; THUJA OCCIDENTALIS LEAFY TWIG 4 [hp_X]/1 mL; THYMOL 6 [hp_X]/1 mL; THYMUS SERPYLLUM WHOLE 6 [hp_X]/1 mL; ARSENIC TRIIODIDE 6 [hp_X]/1 mL; ASTERIAS RUBENS 12 [hp_X]/1 mL; BUFO BUFO CUTANEOUS GLAND 12 [hp_X]/1 mL; HUMAN BREAST TUMOR CELL 16 [hp_X]/1 mL; ARSENIC TRIBROMIDE 20 [hp_X]/1 mL; SHARK CARTILAGE 8 [hp_C]/1 mL; STRYCHNOS WALLICHIANA BARK 9 [hp_C]/1 mL
INACTIVE INGREDIENTS: WATER; ALCOHOL

DRUG FACTS:

ACTIVE INGREDIENTS:

Sabal Serrulata 3X, 6X, Arnica Montana 3X, 6X, 12X, 30X, Cholinum 4X, Thuja Occidentalis 4X, 6X, 12X, 30X, Thymolum 6X, Thymus Serpyllum 6X, 12X, 30X, Arsenicum Iodatum 6X, 12X, 30X, 100X, Asterias Rubens 12X, Bufo Rana 12X, 30X, Carcinosin 16X, 30X, 200X, Arsenicum Bromatum 20X, 30X, 100X, Shark Cartilage 8C, 12C, 30C, 60C, 100C, Hoang Nan 9C.

PURPOSE:

Provides potentized homeo-nutritional support to open enzymatic channels at the cellular level.†

†Claims based on traditional homeopathic practice, not accepted medical evidence. Not FDA evaluated.

WARNINGS:

Professional Use Only

If pregnant or breast-feeding, ask a health professional before use.

In case of overdose, get medical help or contact a Poison Control Center right away.

If condition worsens, seek medical attention.

KEEP OUT OF REACH OF CHILDREN

Do not use if tamper evident seal is broken or missing.

Store in a cool place after opening

KEEP OUT OF REACH OF CHILDREN:

In case of overdose, get medical help or contact a Poison Control Center right away.

DIRECTIONS:

Adults 1 to 2 teaspoons one to two times daily. Children under twelve one half adult dosage. Consult a physician for use in children under 12 years of age.

INDICATIONS:

Provides potentized homeo-nutritional support to open enzymatic channels at the cellular level.†

†Claims based on traditional homeopathic practice, not accepted medical evidence. Not FDA evaluated.

INACTIVE INGREDIENTS:

Alcohol USP 20%, Purified Water USP.

QUESTIONS:

MANUFACTURED EXCLUSIVELY FOR

NUTRITIONAL SPECIALTIES, INC.

PO BOX 97227

PITTSBURG, PA 15229

www.phpltd.com

PACKAGE LABEL DISPLAY:

Professional

Health Products

HOMEOPATHIC

NDC 83027-0033-1

CELLULAR

LIQUESCENCE

4 FL. OZ (120 ml)